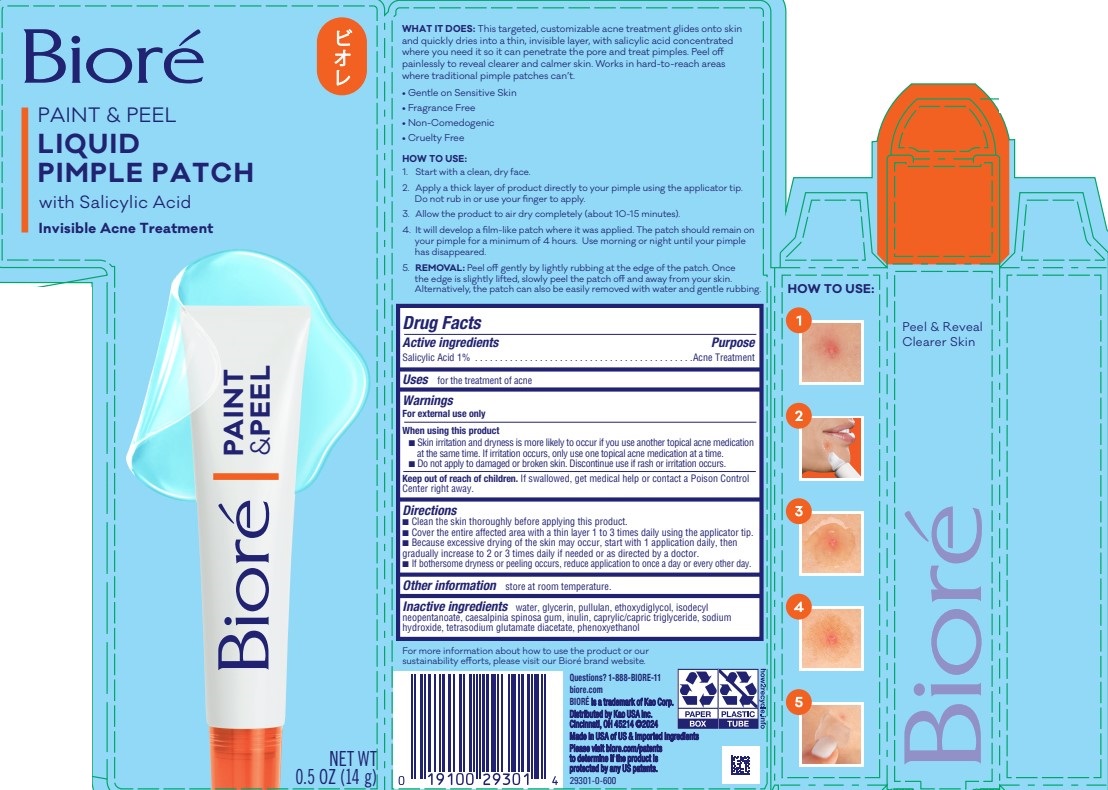 DRUG LABEL: Biore
NDC: 10596-199 | Form: LIQUID
Manufacturer: Kao USA Inc.
Category: otc | Type: HUMAN OTC DRUG LABEL
Date: 20250831

ACTIVE INGREDIENTS: SALICYLIC ACID 1 g/100 g
INACTIVE INGREDIENTS: PULLULAN; ISODECYL NEOPENTANOATE; GLYCERIN; WATER; TETRASODIUM GLUTAMATE DIACETATE; CAPRYLIC/CAPRIC TRIGLYCERIDE; PHENOXYETHANOL; CAESALPINIA SPINOSA GUM; INULIN; ETHOXYDIGLYCOL; SODIUM HYDROXIDE

Biore Paint & Peel Liquid Pimple Patch

Active ingredients

Salicylic Acid 1%

Purpose

Acne treatment

INDICATIONS AND USAGE

Uses for the treatment of acne

Warnings

For external use only

When using this product

- Skin irritation and dryness is more likely to occur if you use another topical acne medication at the same time. If irritation occurs, only use one topical acne medication at a atime.
- Do not apply to damaged or brooken skin. Discontinue use if rash or irritation occurs.

Keep out of reach of children. If swallowed, get medical help of contact a Poison Control Center right away.

Directions

- Clean the skin thoroughly before applying this product.
- Cover the entire affected area with a thin layer 1 to 3 times daily using the applicator tip.
- Because excessive drying of the skin may occur, start with 1 application daily, then gradually increase to 2 or 3 times daily if needed or as directed by a doctor.
- If bothersome dryness or peeling occurs, reduce application to once a day or every other day.

Other information

store at room temperature

INACTIVE INGREDIENT

Inactive ingredients water, glycerin, pullulan, ethoxydiglycol, isodecyl neopentanoate, caesalpinia spinosa gum, inulin, capryllic/capric triglyceride, sodium hydroxide, tetrasodium glutamate diacetate, phenoxyethanol

Questions? 1-888-BIORE-11

biore.com

Biore is a trademark of Kao Corp.

Distributed by Kao USA Inc.

Cincinnati, OH 45214 ©2024

Made in USA of US & imported ingredients

PACKAGE LABEL

Biore

PAINT & PEEL

LIQUID

PIMPLE PATCH

with Salicylic Acid

Invisible Acne Treatment

NET WT

0.5 OZ (14 g)